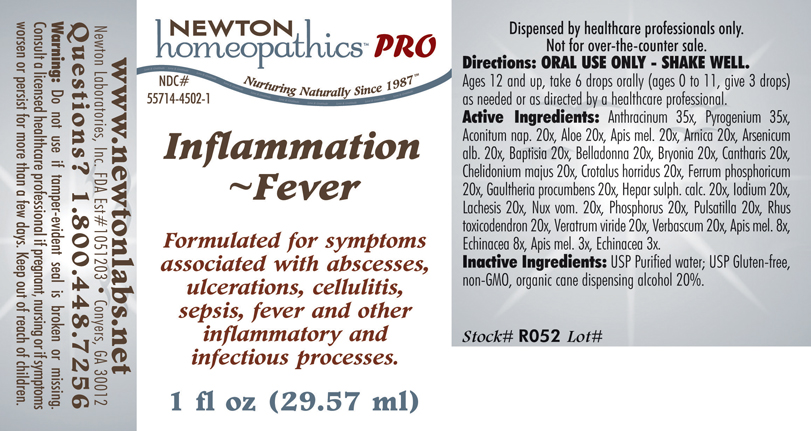 DRUG LABEL: Inflammation - Fever 
NDC: 55714-4502 | Form: LIQUID
Manufacturer: Newton Laboratories, Inc.
Category: homeopathic | Type: HUMAN PRESCRIPTION DRUG LABEL
Date: 20110601

ACTIVE INGREDIENTS: Bacillus Anthracis Immunoserum Rabbit 35 [hp_X]/1 mL; Rancid Beef 35 [hp_X]/1 mL; Aconitum Napellus 20 [hp_X]/1 mL; Aloe 20 [hp_X]/1 mL; Apis Mellifera 20 [hp_X]/1 mL; Arnica Montana 20 [hp_X]/1 mL; Arsenic Trioxide 20 [hp_X]/1 mL; Baptisia Tinctoria Root 20 [hp_X]/1 mL; Atropa Belladonna 20 [hp_X]/1 mL; Bryonia Alba Root 20 [hp_X]/1 mL; Lytta Vesicatoria 20 [hp_X]/1 mL; Chelidonium Majus 20 [hp_X]/1 mL; Crotalus Horridus Horridus Venom 20 [hp_X]/1 mL; Ferrosoferric Phosphate 20 [hp_X]/1 mL; Gaultheria Procumbens Top 20 [hp_X]/1 mL; Calcium Sulfide 20 [hp_X]/1 mL; Iodine 20 [hp_X]/1 mL; Lachesis Muta Venom 20 [hp_X]/1 mL; Strychnos Nux-vomica Seed 20 [hp_X]/1 mL; Phosphorus 20 [hp_X]/1 mL; Pulsatilla Vulgaris 20 [hp_X]/1 mL; Toxicodendron Pubescens Leaf 20 [hp_X]/1 mL; Veratrum Viride Root 20 [hp_X]/1 mL; Verbascum Thapsus 20 [hp_X]/1 mL; Echinacea, Unspecified 8 [hp_X]/1 mL
INACTIVE INGREDIENTS: Alcohol

Inflammation - Fever

INDICATIONS & USAGE SECTION

Inflammation - Fever Formulated for symptoms associated with abscesses, ulcerations, cellulitis, sepsis, fever and other inflammatory and infectious processes.

DOSAGE & ADMINISTRATION SECTION

Directions: ORAL USE ONLY - SHAKE WELL. Ages 12 and up, take 6 drops orally (ages 0 to 11, give 3 drops) as needed or as directed by a healthcare professional.

ACTIVE INGREDIENT SECTION

Anthracinum 35x, Pyrogenium 35x, Aconitum nap. 20x, Aloe 20x, Apis mel. 20x, Arnica 20x, Arsenicum alb. 20x, Baptisia 20x, Belladonna 20x, Bryonia 20x, Cantharis 20x, Chelidonium majus 20x, Crotalus horridus 20x, Ferrum phosphoricum 20x, Gaultheria procumbens 20x, Hepar sulph. calc. 20x, Iodium 20x, Lachesis 20x, Nux vom. 20x, Phosphorus 20x, Pulsatilla 20x, Rhus toxicodendron 20x, Veratrum viride 20x, Verbascum 20x, Apis mel. 8x, Echinacea 8x, Apis mel. 3x, Echinacea 3x.

PURPOSE SECTION

Formulated for symptoms associated with abscesses, ulcerations, cellulitis, sepsis, fever and other inflammatory and infectious processes.

INACTIVE INGREDIENT SECTION

Inactive Ingredients: USP Purified Water; USP Gluten-free, non-GMO, organic cane dispensing alcohol 20%.

QUESTIONS? SECTION

www.newtonlabs.net Newton Laboratories, Inc. FDA Est # 1051203 - Conyers, GA 30012
Questions? 1.800.448.7256

WARNINGS SECTION

Warning: Do not use if tamper - evident seal is broken or missing. Consult a licensed healthcare professional if pregnant, nursing or if symptoms worsen or persist for more than a few days. Keep out of reach of children.

PREGNANCY OR BREAST FEEDING SECTION

Consult a licensed healthcare professional if pregnant or nursing or if symptoms worsen or persist for more than a few days.

KEEP OUT OF REACH OF CHILDREN SECTION

Keep out of reach of children.